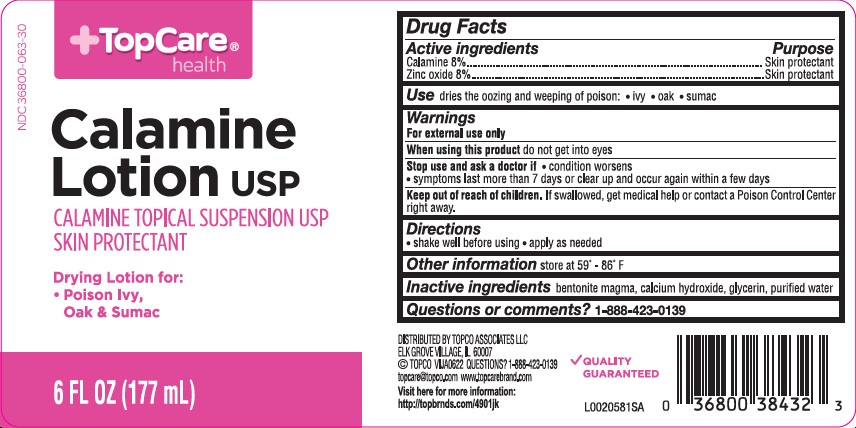 DRUG LABEL: Calamine
NDC: 36800-063 | Form: LOTION
Manufacturer: Topco Associates LLC
Category: otc | Type: HUMAN OTC DRUG LABEL
Date: 20260213

ACTIVE INGREDIENTS: FERRIC OXIDE RED 80 mg/1 mL; ZINC OXIDE 80 mg/1 mL
INACTIVE INGREDIENTS: BENTONITE; CALCIUM HYDROXIDE; GLYCERIN; WATER

Top Care 063.001/063AA
Calamine Lotion

Active ingredents

Calamine 8%
Zinc oxide 8%

Purpose

Skin Protectant

Use

dries the oozing and weeping of poison:

- ivy
- oak
- sumac

Warnings

For external use only

When using this product

Do not get into eyes

Stop use and ask a doctor if

- condition worsens
- symptoms last more than 7 days or clear up and occur again within a few days

Keep out of reach of children.

If swallowed, get medical help or contact a Poison Control Center right away.

Directions

- shake well before using
- apply as needed

Other information

store at 59⁰ - 86⁰ F

Inactive ingredients

bentonite magma, calcium hydroxide, glycerin, purified water

Questions or comments?

1-888-423-0139

ADVERSE REACTION

DISTRIBUTED BY TOPCO ASSOCIATES LLC

ELK GROVE VILLAGE, IL 60007

©TOPCO VIJA0622 QUESTIONS? 1-888-423-0139

topcare@topco.com www.topcarebrand.com

Visit here for more information:

http://topbrnds.com/4901jk

QUALITY GUARANTEED

principal display panel

NDC 36800-063-30

TopCare®health

Calamine Lotion USP

CALAMINE TOPICAL SUSPENSION USP

SKIN PROTECTANT

Drying Lotion for:

- Poison Ivy, Oak & Sumac

6 FL OZ (177 mL)